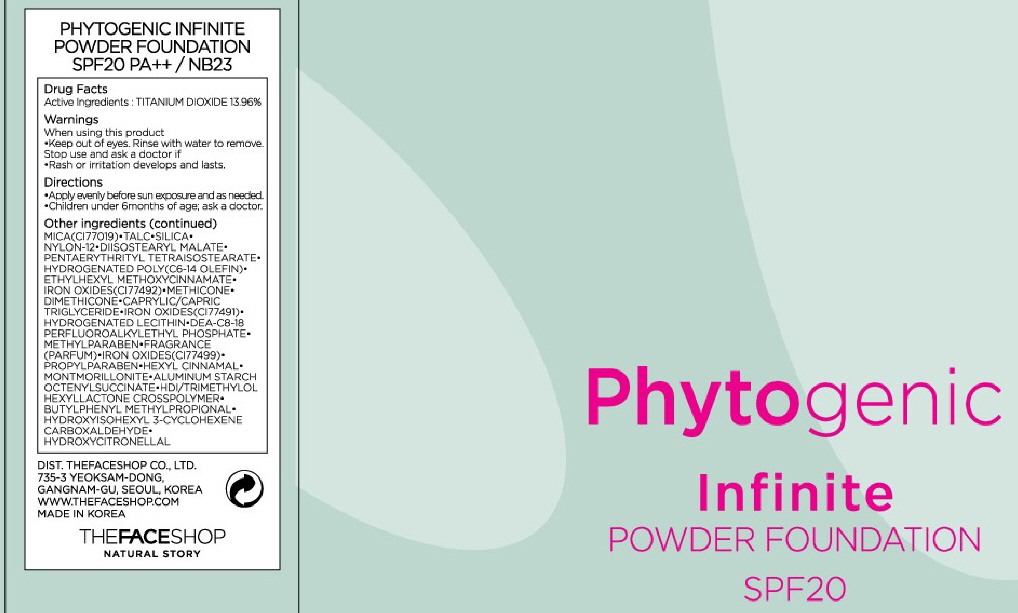 DRUG LABEL: PHYTOGENIC INFINITE POWDER FOUNDATION
NDC: 51523-034 | Form: POWDER
Manufacturer: THEFACESHOP CO., LTD.
Category: otc | Type: HUMAN OTC DRUG LABEL
Date: 20100929

ACTIVE INGREDIENTS: TITANIUM DIOXIDE 1.68 g/12 g

Drug Facts

Active Ingredient: TITANIUM DIOXIDE

Inactive Ingredients:

MICA, TALC, SILICA, NYLON-12, DIISOSTEARYL MALATE, PENTAERYTHRITYL TETRAISOSTEARATE, HYDROGENATED POLY(C6-14 OLEFIN), ETHYLHEXYL METHOXYCINNAMATE,
METHICONE, DIMETHICONE, CAPRYLIC/CAPRIC TRIGLYCERIDE, IRON OXIDES(CI77491), HYDROGENATED LECITHIN, DEA-C8-18 PERFLUOROALKYLETHYL PHOSPHATE,
METHYLPARABEN, FRAGRANCE, IRON OXIDES(CI77499), PROPYLPARABEN, HEXYL CINNAMAL, MONTMORILLONITE, ALUMINUM STARCH OCTENYLSUCCINATE, HDI/TRIMETHYLOL HEXYLLACTONE CROSSPOLYMER, BUTYLPHENYL METHYLPROPIONAL, HYDROXYISOHEXYL 3-CYCLOHEXENE CARBOXALDEHYDE, HYDROXYCITRONELLAL

Warnings:
When using this product
Keep out of eyes. Rinse with water to remove.
Stop use and ask a doctor if
Rash or irritation develops and lasts.
Directions:
Apply evenly before sun exposure and as needed.
Children under 6months of age; ask a doctor.